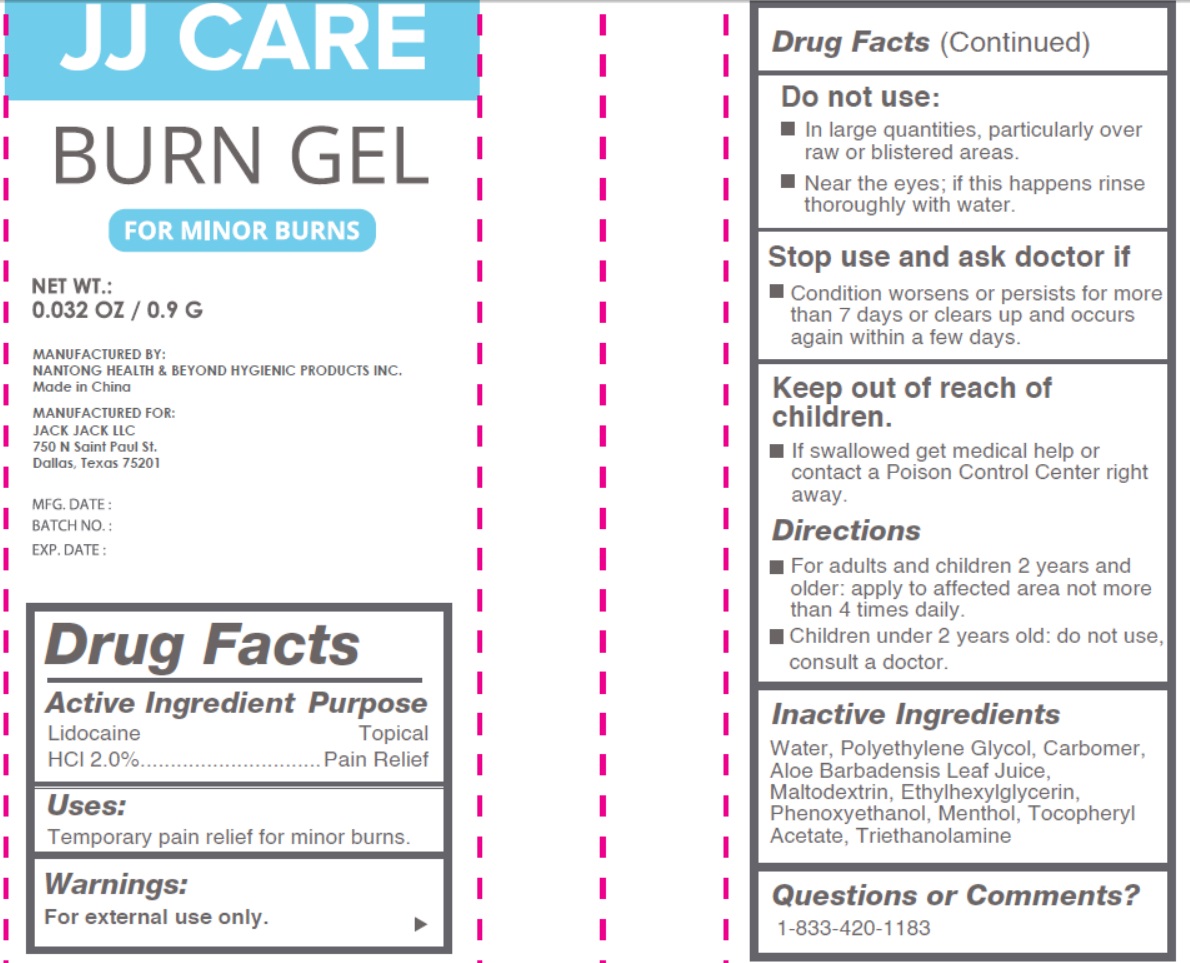 DRUG LABEL: Burn
NDC: 43473-048 | Form: GEL
Manufacturer: Nantong Health & Beyond Hygienic Products Inc.
Category: otc | Type: HUMAN OTC DRUG LABEL
Date: 20240115

ACTIVE INGREDIENTS: LIDOCAINE HYDROCHLORIDE 20 mg/1 g
INACTIVE INGREDIENTS: ALOE VERA LEAF; CARBOMER HOMOPOLYMER, UNSPECIFIED TYPE; ETHYLHEXYLGLYCERIN; MALTODEXTRIN; MENTHOL; POLYETHYLENE GLYCOL, UNSPECIFIED; PHENOXYETHANOL; TROLAMINE; .ALPHA.-TOCOPHEROL ACETATE; WATER

43473-048 JJ Care Burn Gel

Active Ingredient

Lidocaine HCl 2.0%

Purpose

Topical Pain Relief

Uses

Temporary pain relief for minor burns.

Warnings:

For external use only

Do not use

- ln large quantities, particularly over raw or blistered areas.
- Near the eyes; if this happens rinse thoroughly with water.

Stop use and ask doctor if

- Condition worsens or persists for more than 7 days or clears up and occurs again within a few days.

Keep out of reach of children.

If swallowed get medical help or contact a Poison Control Center right away.

Directions

- For adults and children 2 years and older: apply to affected area not more than 4 times daily.
- Children under 2 years old: do not use, consult a doctor.

lnactive lngredients

Water, Polyethylene Glycol, Carbomer, Aloe Barbadensis Leaf Juice, Maltodextrin, Ethylhexylglycerin, Phenoxyethanol, Menthol, Tocopheryl Acetate, Triethanolamine

Questions or Comments?

1-833-420-1183